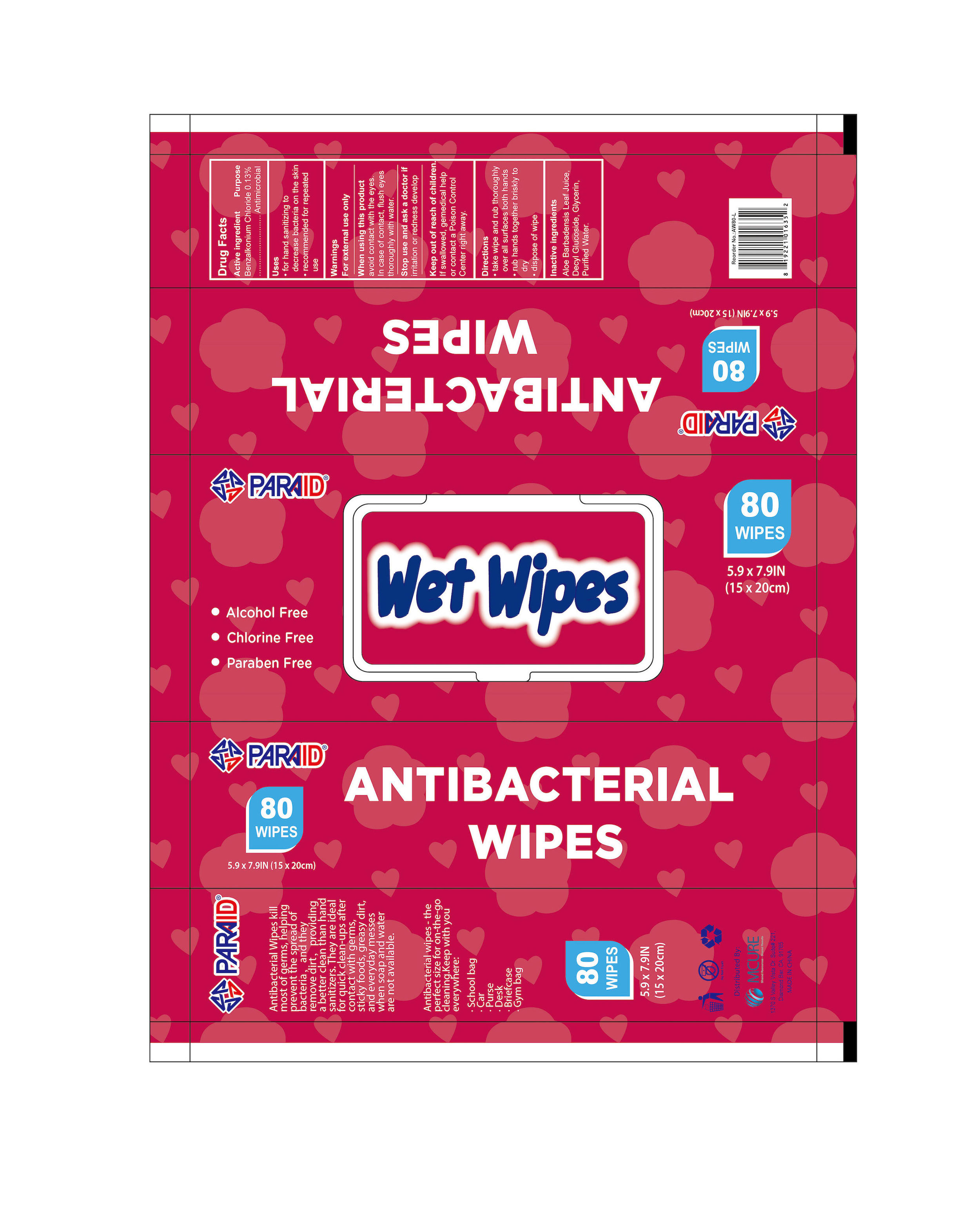 DRUG LABEL: ANTIBACTERIAL WIPES
NDC: 52486-081 | Form: CLOTH
Manufacturer: MCURE HEALTH SOLUTIONS INC.
Category: otc | Type: HUMAN OTC DRUG LABEL
Date: 20201216

ACTIVE INGREDIENTS: BENZALKONIUM CHLORIDE 13 mg/100 mL
INACTIVE INGREDIENTS: GLYCERIN; WATER; DECYL GLUCOSIDE

Active ingredient Purpose

Benzalkonium Chloride 0.13% ........................... Antimicrobial

Uses

- for hand sanitizing to decrease bacteria on the skin
- recommended for repeated use

Warnings

For external use only

When using this product avoid contact with the eyes. In case of contact, flush eyes thoroughly with water.

Stop use and ask a doctor if irritation or redness develop.

Keep out of reach of children. If swallowed, gemedical help or contact a Poison Control Center right away.

Directions

- take wipe and rub thoroughly over all surfaces both hands
- rub hands together briskly to dry
- dispose of wipe

Inactive ingredients

Aloe Barbadensis Leaf Juice, Decyl Glucoside, Glycerin, Purified Water.

Uses

for hand sanitizing to decrease bacteria on the skin
recommended for repeated use

PACKAGE LABEL

80pcs/box NDC:52486-081-01